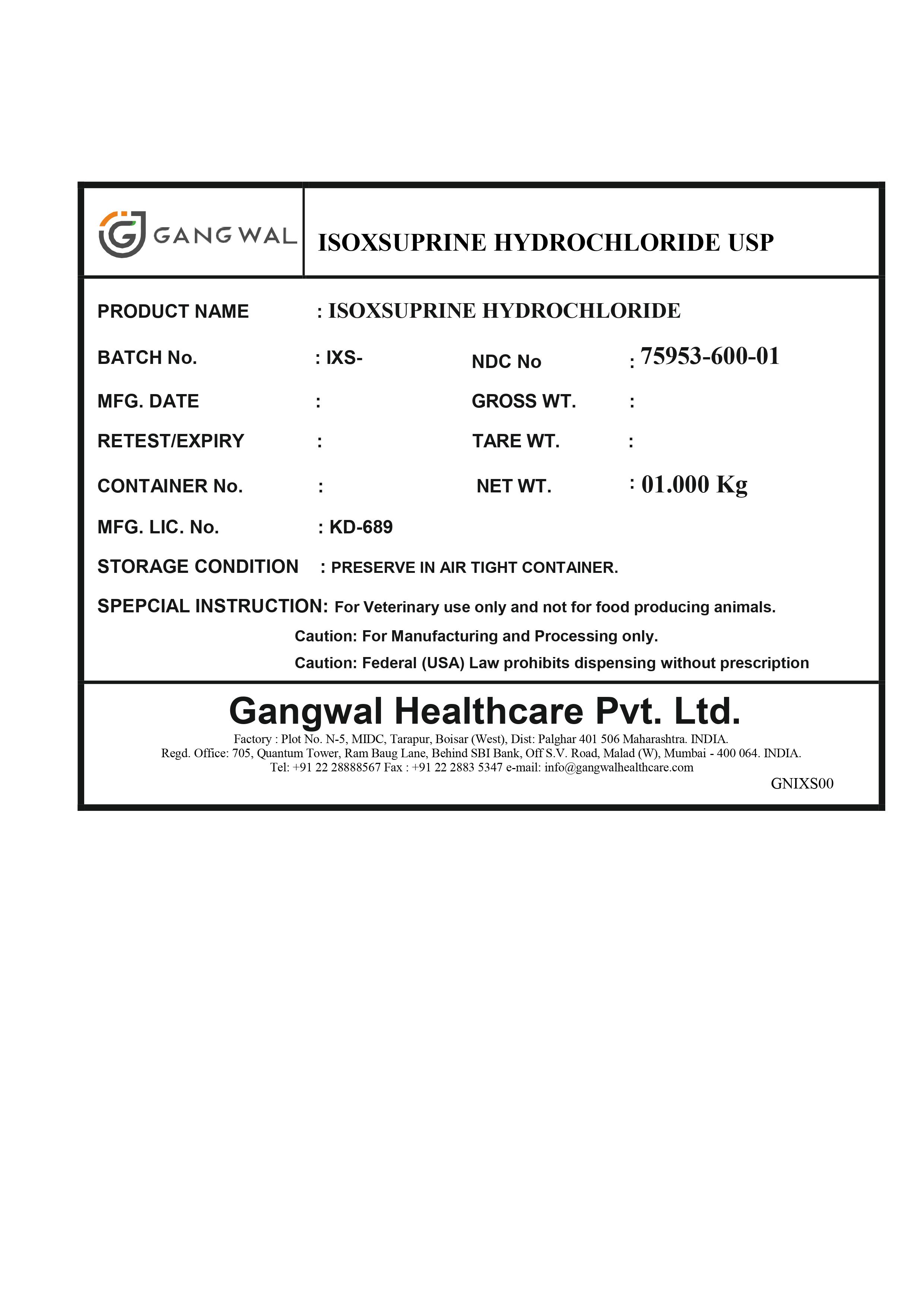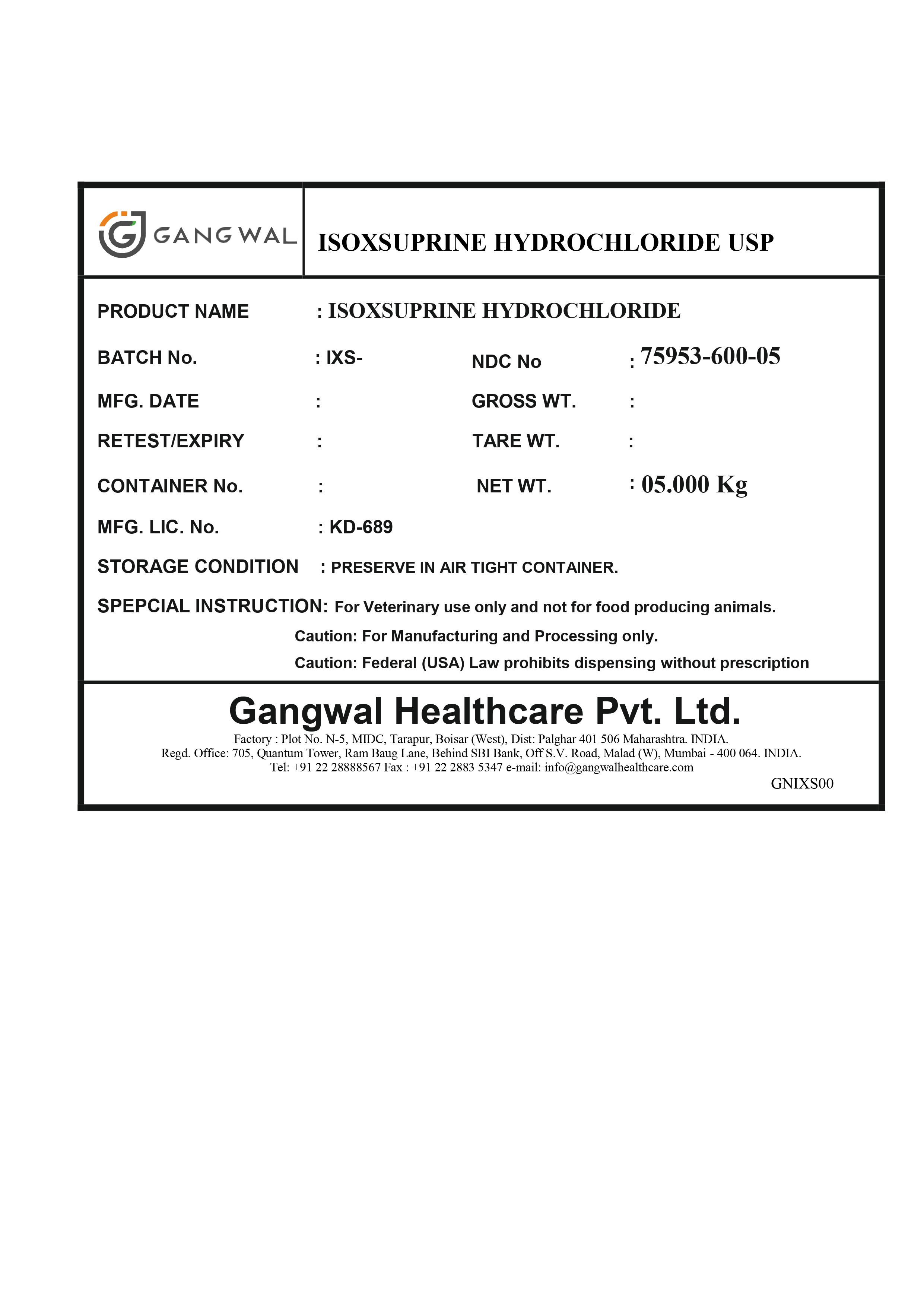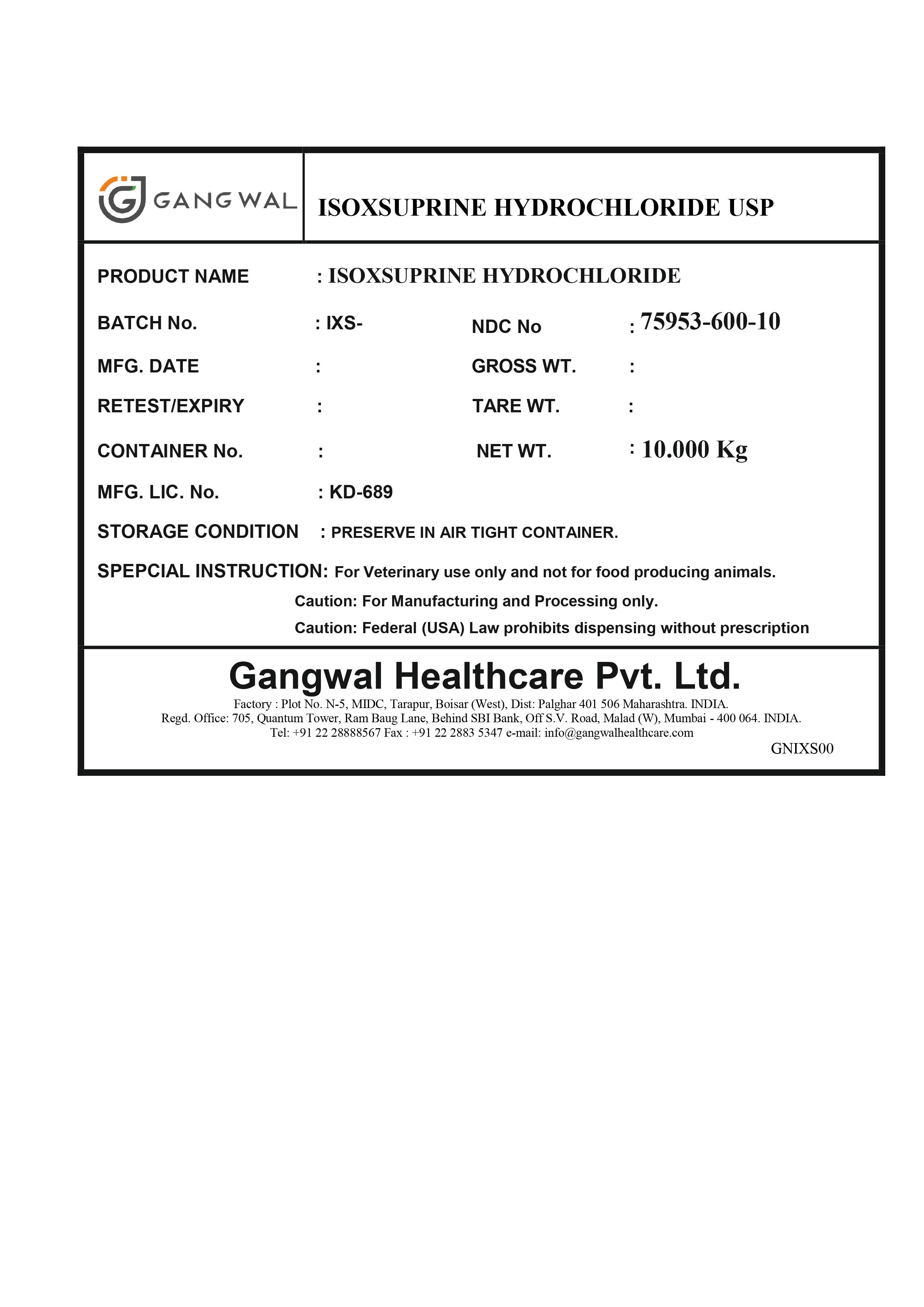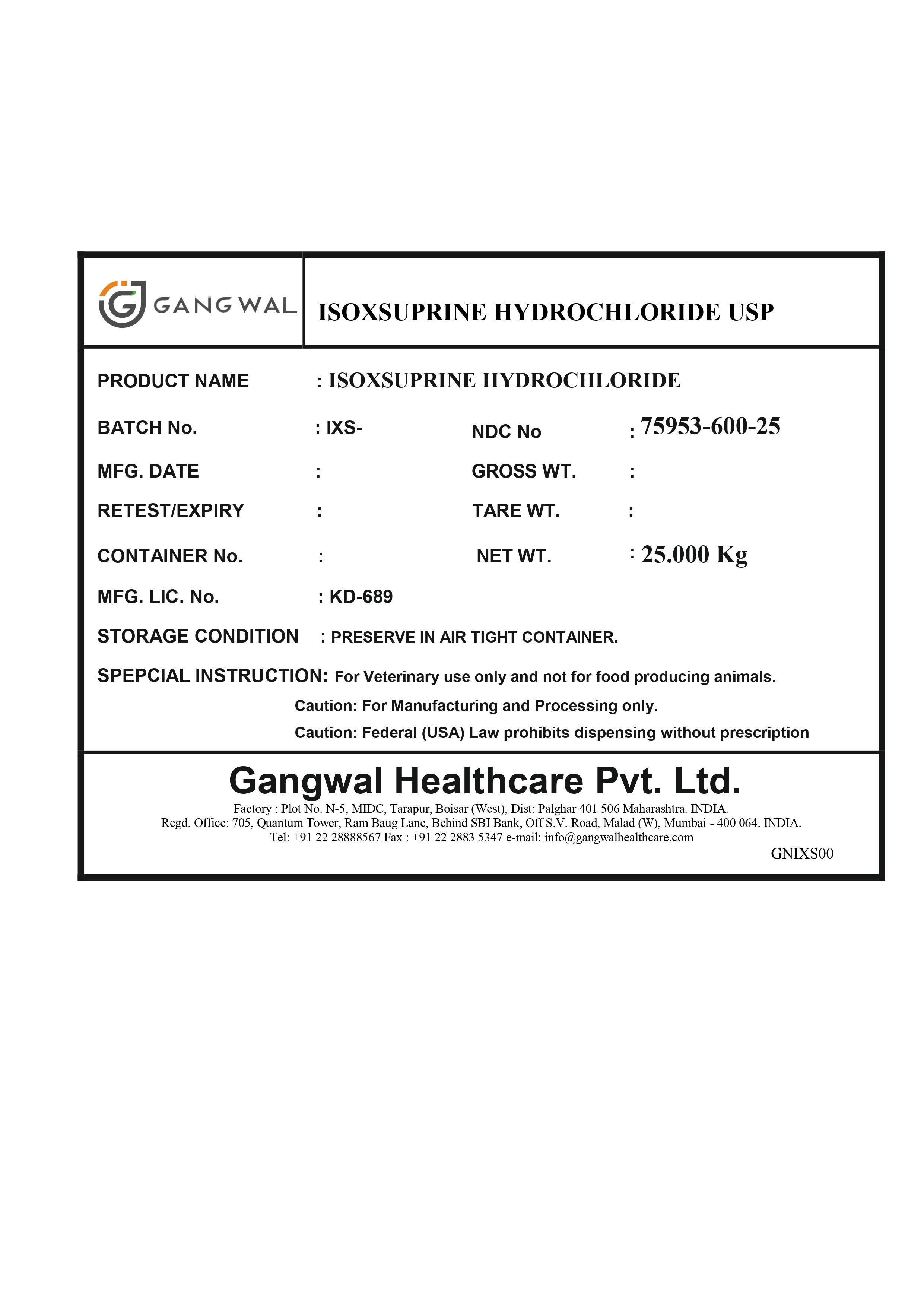 DRUG LABEL: Isoxsuprine Hydrochloride
NDC: 75953-600 | Form: POWDER
Manufacturer: Gangwal Healthcare Private Limited
Category: other | Type: BULK INGREDIENT - ANIMAL DRUG
Date: 20220322

ACTIVE INGREDIENTS: ISOXSUPRINE HYDROCHLORIDE 1 kg/1 kg

ISOXSUPRINE HYDROCHLORIDE USP